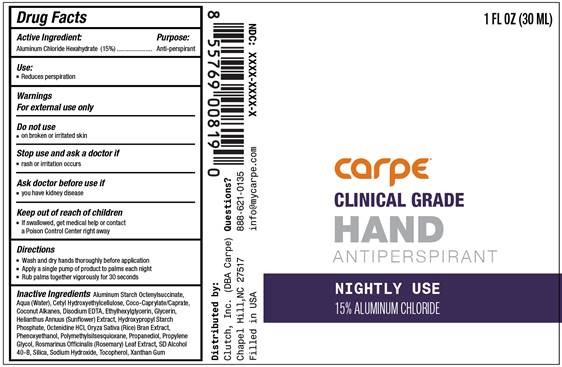 DRUG LABEL: Hand Antiperspirant Nightly Use
NDC: 74307-008 | Form: CREAM
Manufacturer: Clutch Inc
Category: otc | Type: HUMAN OTC DRUG LABEL
Date: 20260226

ACTIVE INGREDIENTS: ALUMINUM CHLORIDE 15 g/100 mL
INACTIVE INGREDIENTS: POLYMETHYLSILSESQUIOXANE (4.5 MICRONS); SILICON DIOXIDE; EDETATE DISODIUM; GLYCERIN; HELIANTHUS ANNUUS FLOWERING TOP; OCTENIDINE HYDROCHLORIDE; ALUMINUM STARCH OCTENYLSUCCINATE; COCONUT ALKANES; COCOYL CAPRYLOCAPRATE; WATER; CETYL HYDROXYETHYLCELLULOSE (350000 MW); TOCOPHEROL; XANTHAN GUM; ROSEMARY; PROPYLENE GLYCOL; ETHYLHEXYLGLYCERIN; RICE BRAN; PHENOXYETHANOL; PROPANEDIOL; SODIUM HYDROXIDE

HAND ANTIPERSPIRANT NIGHTLY USE

Active Ingredient Purpose

Aluminum Chloride Hexahydrate (15%) Anti-perspirant

Use

- reduces perspiration

KEEP OUT OF REACH OF CHILDREN

Keep out reach of children.If swallowed get medical help or contact a Poison Control Center right away

Stop use and ask a doctor ifrash or irritation occurs

Warnings

For external use only.

Do not useon broken or irritated skin

Ask a doctor before use ifyou have kidney disease.

Directions

Wash and dry hands thoroughly before application
Apply a single pump of product to palms each morning
Rub palms together vigorously for 30 seconds

INACTIVE INGREDIENT

Inactive IngredientsAluminum Starch Octenylsuccinate, Aqua (water), Cetyl Hydroxyethylcellulose, Coco-Caprylate/Caprate,Coconut Alkanes, Disodium EDTA, Ethylhexylglycerin, Glycerin, Helianthus Annuus (Suflower) Extract, Hydroxypropyl Starch Phosphate, Octenidine HCL, Oryza Sativa (Rice) Bran Extract, Phenoxyethanol, Polymethylsilsesquioxane, Propanediol, Propylene Glycol, Rosmarinus Officinalis (Rosemary) Leaf Extract, SD Alcohol 40-B, SIlica, Sodium Hydroxide, Tocopherol, Xanthan Gum

PACKAGE LABEL

Carpe

Clinical Grade HAND

Antiperspirant

Nightly Use

15% Aluminum Chloride